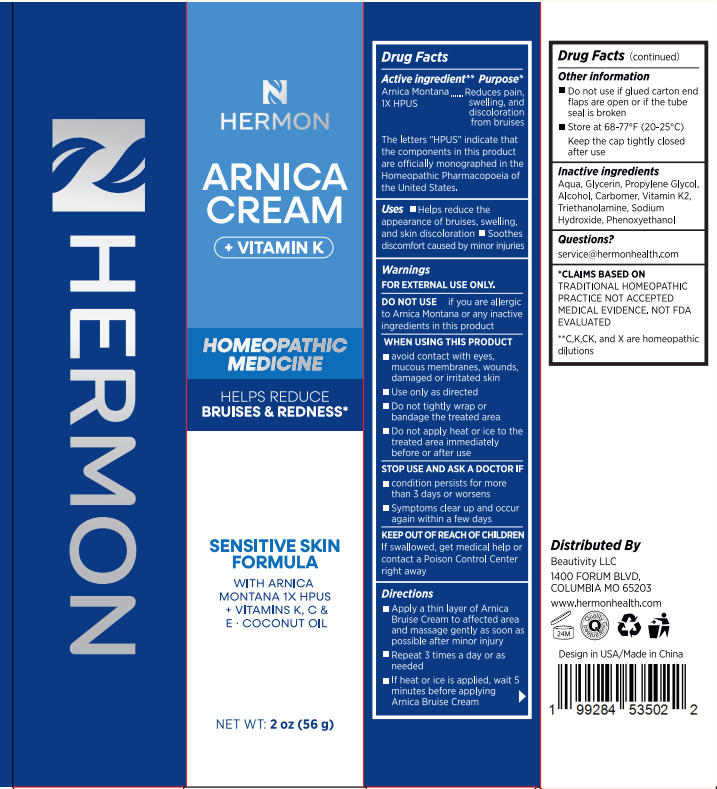 DRUG LABEL: Hermon Arnica Cream sensitive skin formula 2 oz
NDC: 85398-015 | Form: CREAM
Manufacturer: Beautivity LLC
Category: homeopathic | Type: HUMAN OTC DRUG LABEL
Date: 20250925

ACTIVE INGREDIENTS: ARNICA MONTANA 1 [hp_X]/56 g
INACTIVE INGREDIENTS: AQUA; TRIETHANOLAMINE; PROPYLENE GLYCOL; SODIUM HYDROXIDE; ALCOHOL; GLYCERIN; CARBOMER; MENAQUINONE 6; PHENOXYETHANOL

Initial Drug Listing - Hermon Arnica Cream sensitive skin formula 2 oz

ACTIVE INGREDIENT

Arnica Montana 1X HPUS

The letters "HPUS" indicate that the components in this productare officially monographed in the Homeopathic Pharmacopoeia of the United States.

PURPOSE

Reduces pain, swelling, anddiscolorationfrom bruises

DOSAGE AND ADMINISTRATION

- Helps reduce the appearance of bruises, swelling,and skin discoloration
- Soothes discomfort caused by minor injuries

WARNINGS

FOR EXTERNAL USE ONLY.

DO NOT USE

if you are allergic to Arnica Montana or any inactive ingredients in this product.

WHEN USING

- avoid contact with eyes,mucous membranes, wounds,damaged or irritated skin
- Use only as directed
- Do not tightly wrap or bandage the treated area
- Do not apply heat or ice to the treated area immediately before or after use

ASK DOCTOR

- condition persists for more than 3 days or worsens
- Symptoms clear up and occur again within a few days

KEEP OUT OF REACH OF CHILDREN

If swallowed, get medical help orcontact a Poison Control Center right away

INDICATIONS AND USAGE

- Apply a thin layer of Arnica Bruise Cream to affected area and massage gently as soon as possible after minor injury
- Repeat 3 times a day or as needed
- lf heat or ice is applied, wait 5 minutes before applying Arnica Bruise Cream

- Do not use if glued carton end flaps are open or if the tube seal is broken
- Store at 68-77°F(20-25°C)
- Keep the cap tightly closed after use

INACTIVE INGREDIENT

Aqua, Glycerin, Propylene Glycol, Alcohol, Carbomer, Vitamin K2, Triethanolamine, Sodium Hydroxide, Phenoxyethanol

QUESTIONS

service@hermonhealth.com